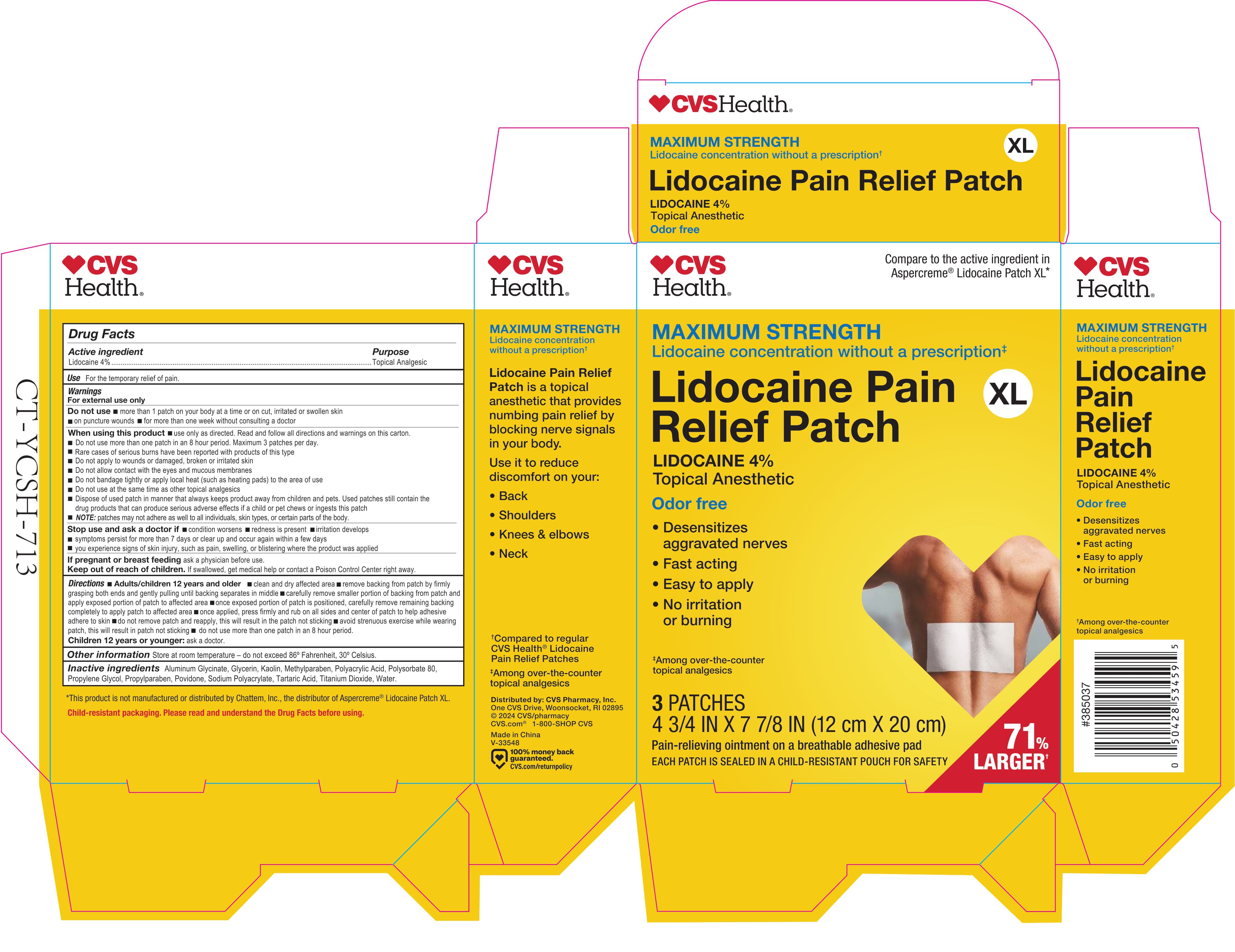 DRUG LABEL: CVS Pain Relief Lidocaine XL
NDC: 51316-286 | Form: PATCH
Manufacturer: CVS Pharmacy
Category: otc | Type: HUMAN OTC DRUG LABEL
Date: 20260212

ACTIVE INGREDIENTS: LIDOCAINE 40 mg/1 g
INACTIVE INGREDIENTS: POVIDONE; KAOLIN; PROPYLPARABEN; TARTARIC ACID; WATER; GLYCERIN; ALUMINUM GLYCINATE; PROPYLENE GLYCOL; METHYLPARABEN; POLYSORBATE 80; SODIUM POLYACRYLATE (8000 MW); POLYACRYLIC ACID (8000 MW); TITANIUM DIOXIDE

CVS Pain Relief Patch Lidocaine XL

Active ingredient

Lidocaine 4%

Purpose

Topical Analgesic

Use

For the temporary relief of pain.

Warnings

For external use only

Do not use

- more than 1 patch on your body at a time or on cut, irritated or swollen skin
- on puncture wounds
- for more than one week without consulting a doctor

When using this product

- use only as directed. Read and follow all directions and warnings on this carton.
- Do not use more than one patch in an 8 hour period. Maximum 3 patches per day.
- Rare cases of serious burns have been reported with products of this type
- Do not apply to wounds or damaged, broken or irritated skin
- Do not allow contact with the eyes and mucous membranes
- Do not bandage tightly or apply local heat (such as heating pads) to the area of use
- Do not use at teh same time as other topical analgesics
- Dispose of used patch in manner that always keeps product away from children and pets. Used patches still contain the drug products that can produce serious adverse effects if a child or pet chews or ingests this patch
- NOTE: patches may not adhere as well to all individuals, skin types, or certain parts of the body.

Stop use and ask a doctor if

- condition worsens
- redness is present
- irritation develops
- symptoms persist for more than 7 days or clear up and occur again within a few days
- you experience signs of skin injury, such as pain, swelling, or blistering where the product was applied

If pregnant or breast feeding

ask a physician before use.

Keep out of reach of children.

If swallowed, get medical help or contact a Poison Control Center right away.

Directions

- Adults/children 12 years and older
- clean and dry affected area
- remove backing from patch by firmly grasping both ends and gently pulling until backing separates in middle
- carefully remove smaller portion of backing from patch and apply exposed portion of patch to affected area
- once exposed portion of patch ispositioned, carefully remove remaining backing completely to apply patch to affected area
- once applied, press firmly and rub on all sides and center of patch to help adhesive adhere to skin
- do not remove patch and reapply, this will result in the patch not sticking
- avoid strenuous exercise while wearing patch, this will result in patch not sticking
- do not use more than one patch in an 8 hour period.
- Children 12 years or younger: ask a doctor.

Other information

Store at room temperature - do not exceed 86° Fahrenheit, 30° Celsius.

Inactive ingredients

Aluminum Glycinate, Glycerin, Kaolin, Methylparaben, Polyacrylic Acid, Polysorbate 80, Propylene Glycol, Propylparaben, Povidone, Sodium Polyacrylate, Tartaric Acid, Titanium Dioxide, Water.

Principal Display Panel - 4 3/4 IN X 7 7/8 IN Carton Label

CVS Health®

Compare to the active ingredient in Aspercreme® Lidocaine Patch XL*

Maximum Strength

Lidocaine concentration without a prescription‡

Lidocaine Pain Relief Patch

XL

Lidocaine 4%

Topical Anesthetic

Odor free

- Desensitizes aggravated nerves
- Fast acting
- Easy to apply
- No irritation or burning

‡Among over-the-counter topical analgesics

3 PATCHES

4 3/4 IN X 7 7/8 IN (12 cm X 20 cm)

Pain-relieving ointment on a breathable adhesive pad

EACH PATCH IS SEALED IN A CHILD-RESISTANT POUCH FOR SAFETY

71% LARGER